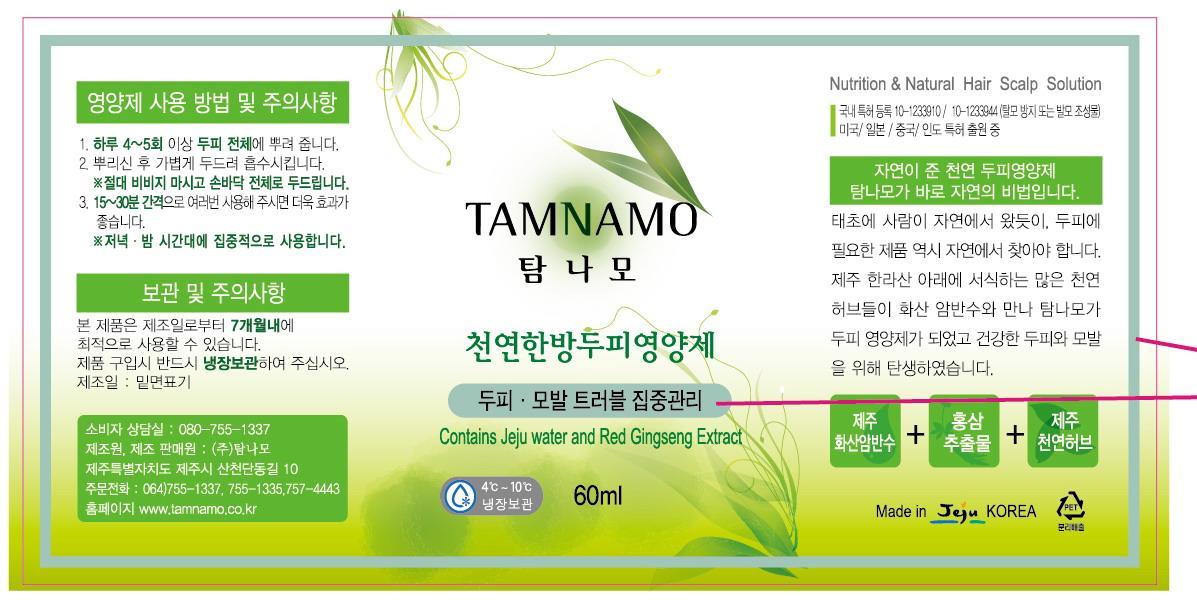 DRUG LABEL: TAMNAMO ESSENTIAL HAIR TONIC
NDC: 60344-3001 | Form: LIQUID
Manufacturer: Tamnamo Co., Ltd
Category: otc | Type: HUMAN OTC DRUG LABEL
Date: 20130826

ACTIVE INGREDIENTS: ASIAN GINSENG 0.03 mg/1 mL
INACTIVE INGREDIENTS: PLATYCLADUS ORIENTALIS LEAF; SAURURUS CHINENSIS WHOLE; POLYGONATUM MULTIFLORUM WHOLE; PULSATILLA KOREANA WHOLE; USNEA BARBATA

Drug Facts

ACTIVE INGREDIENT

red ginseng extract

INACTIVE INGREDIENT

Jeju Water, Red Gingseng Extract, Duchesnea Indica Fruit Extract, Blueberry Extract, Cereus Gandiflorus Extract, Thuja Orientalis Leaf Extract, Black Bean Extract, Saururus Chinensis Leaf/Root Extract, Polygonatum Multiflorum Rhizome/Root Extract, Green Tea Extract, Zanthoxylum Pieperitum Fruit Extract, Pulsatilla Koreana Extract, Usnea Barbata Root Extract

PURPOSE

supplying moisture and nutrient to scalp and hair

keep out of reach of the children

INDICATIONS AND USAGE

shake before use as it is made with oriental medicine materials which can have some sediments
use 3 times daily, preferably at night before bed and after shower. please leave our product on overnight
spray 3~5ml thoroughly all over the scalp
massage gently, using fingertips for few minutes

WARNINGS

if you notice any skin trouble or other unexpected reaction such as rash, irritation discontinue use immediately and ask a doctor
do not expose this product directly to the sun and store in a cool dry place

DOSAGE AND ADMINISTRATION

for external use only